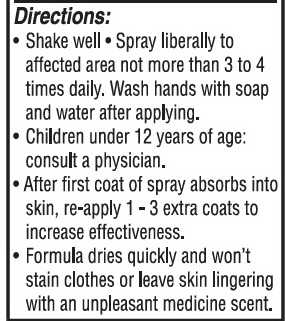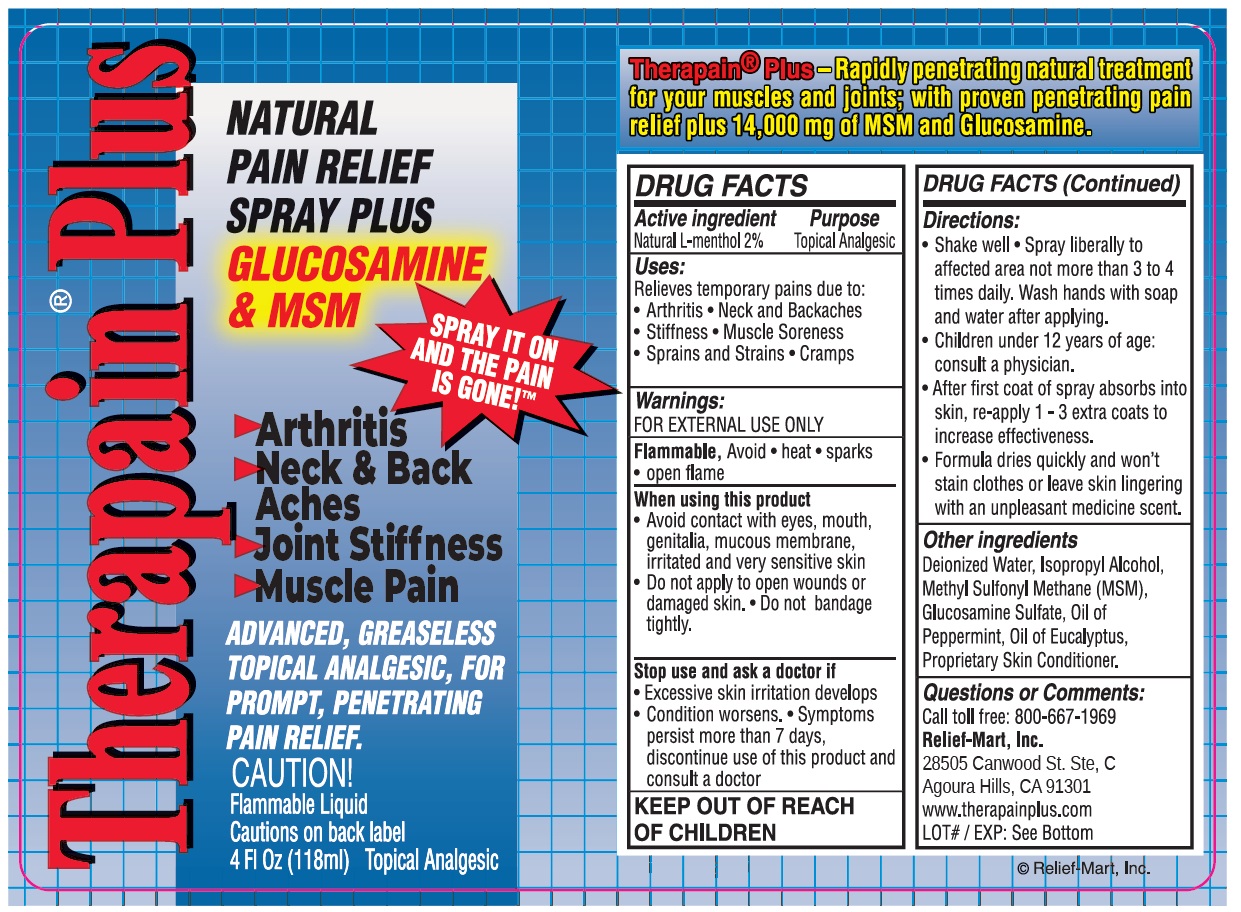 DRUG LABEL: Menthol
NDC: 67285-102 | Form: SPRAY
Manufacturer: Relief-Mart, Inc
Category: otc | Type: HUMAN OTC DRUG LABEL
Date: 20220113

ACTIVE INGREDIENTS: MENTHOL 2 g/100 mL
INACTIVE INGREDIENTS: ISOPROPYL ALCOHOL 34.17 g/100 mL; EUCALYPTUS OIL 0.083 g/100 mL; GLUCOSAMINE SULFATE 1.67 g/100 mL; PEPPERMINT OIL 0.208 g/100 mL; WATER 51.829 g/100 mL; DIMETHYL SULFONE 8.33 g/100 mL; PROPYLENE GLYCOL 1.67 g/100 mL

Therapain Plus Spray NDC 67285-102

Warnings

For external use only. If accidentally ingested contact poison control immediately.

Active Ingredients

Natural L-Menthol 2%

Purpose

Topical Analgesic

Inactive Ingedients

Deionized Water, Isopropyl Alcohol, Oil of Peppermint, Oil of Eucalyptus, Proprietary Skin Conditioner.

Stop use section

Stop use and ask a doctor if

- Excessive skin irritation develops
- Conditions worsens
- Symptoms persist more than 7 days, discontinue use of this product and consult a doctor

Uses

Relieves temporary pain due to

arthiritus

neck and back pains

stiffness

msucle soreness

cramps

sprains and strains

tendonitis

RECENT MAJOR CHANGES

Uploaded revised label and updated the following information:

- Dosage and Administration (Directions)
- Added information on Stop Use and Ask a Doctor if